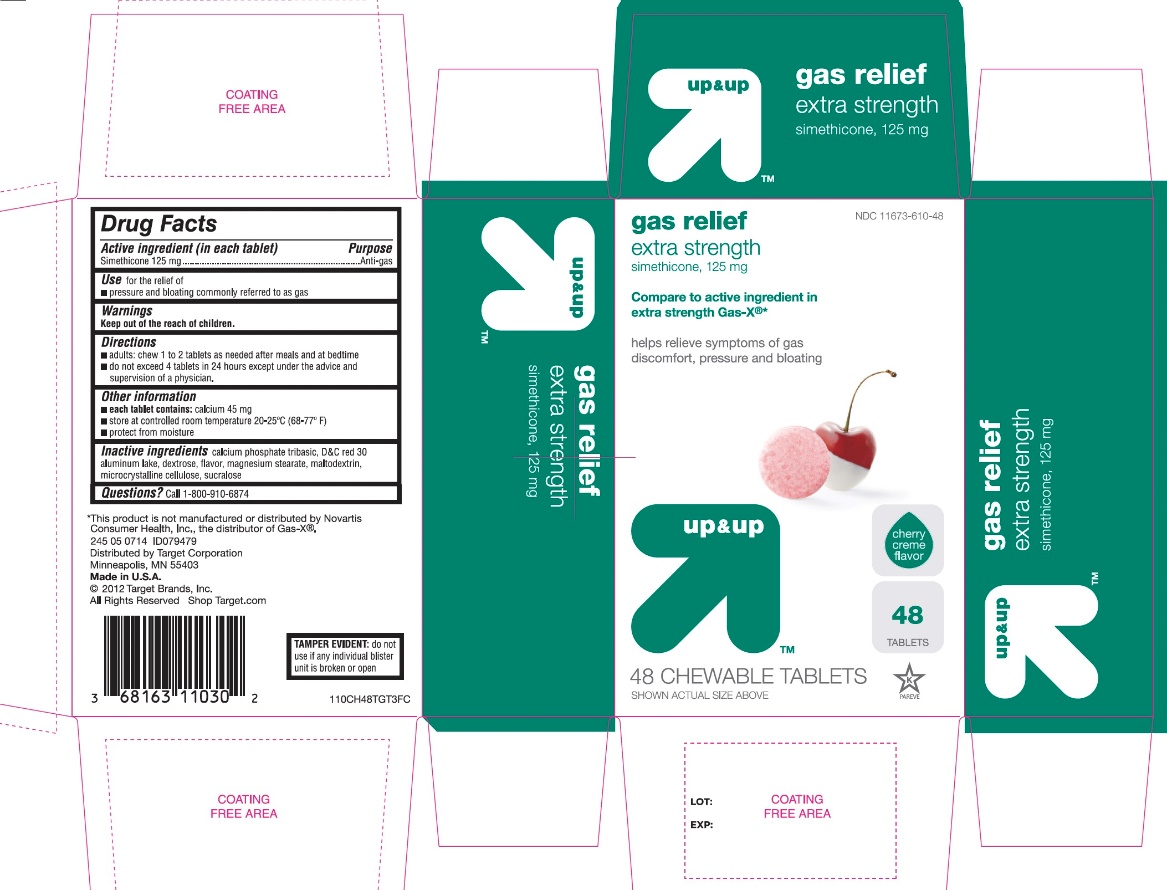 DRUG LABEL: up and up extra strength gas relief chewables

NDC: 11673-610 | Form: TABLET, CHEWABLE
Manufacturer: Target Corporation
Category: otc | Type: HUMAN OTC DRUG LABEL
Date: 20251104

ACTIVE INGREDIENTS: DIMETHICONE, UNSPECIFIED 125 mg/1 1
INACTIVE INGREDIENTS: DEXTROSE, UNSPECIFIED FORM; D&C RED NO. 30; MAGNESIUM STEARATE; MALTODEXTRIN; MICROCRYSTALLINE CELLULOSE; SILICON DIOXIDE; SUCRALOSE; TRIBASIC CALCIUM PHOSPHATE

up and up extra strength gas relief Chewables

Active ingredient (in each tablet)

Simethicone 125 mg

Purpose

Anti-gas

Uses

for the relief of

- pressure and bloating commonly referred to as gas

Directions

- adults: chew 1 or 2 tablets as needed after meals and at bedtime
- do not exceed 4 tablets in 24 hours except under the advice and supervision of a physician

Other information

-
  - each tablet contains:calcium 45 mg
  - store at controlled room temperature 20-25°C (68-77°F)
  - protect from excessive heat and moisture

Inactive ingredients

dextrose, D&C red 30 aluminum lake, flavor, magnesium stearate, maltodextrin, microcrystalline cellulose, silica, sucralose, tribasic calcium phosphate

Questions or comments?

1-866-467-2748

Principal Display Panel

NDC 11673-610-48

Compare toactive ingredient in extra strength Gas-X®*

extra Strength

gas relief chewable

simethicone, 125mg/antigas

- fast relief of gas pressure, bloating and discomfort

Cherry creme flavor

48 COUNT

48 CHEWABLE TABLETS

*This product is not manufactured or distributed by Novartis Consumer Health, Inc., the distributor of Extra Strength GAS-X®.

DO NOT USE IF ANY INDIVIDUAL BLISTER IS BROKEN OR OPEN

245 05 0624 R01 ID285497

Dist. by Target Corp.

Mpls., MN 55403

©2015 Target Brands, Inc.

Shop Target.com

Made in U.S.A.